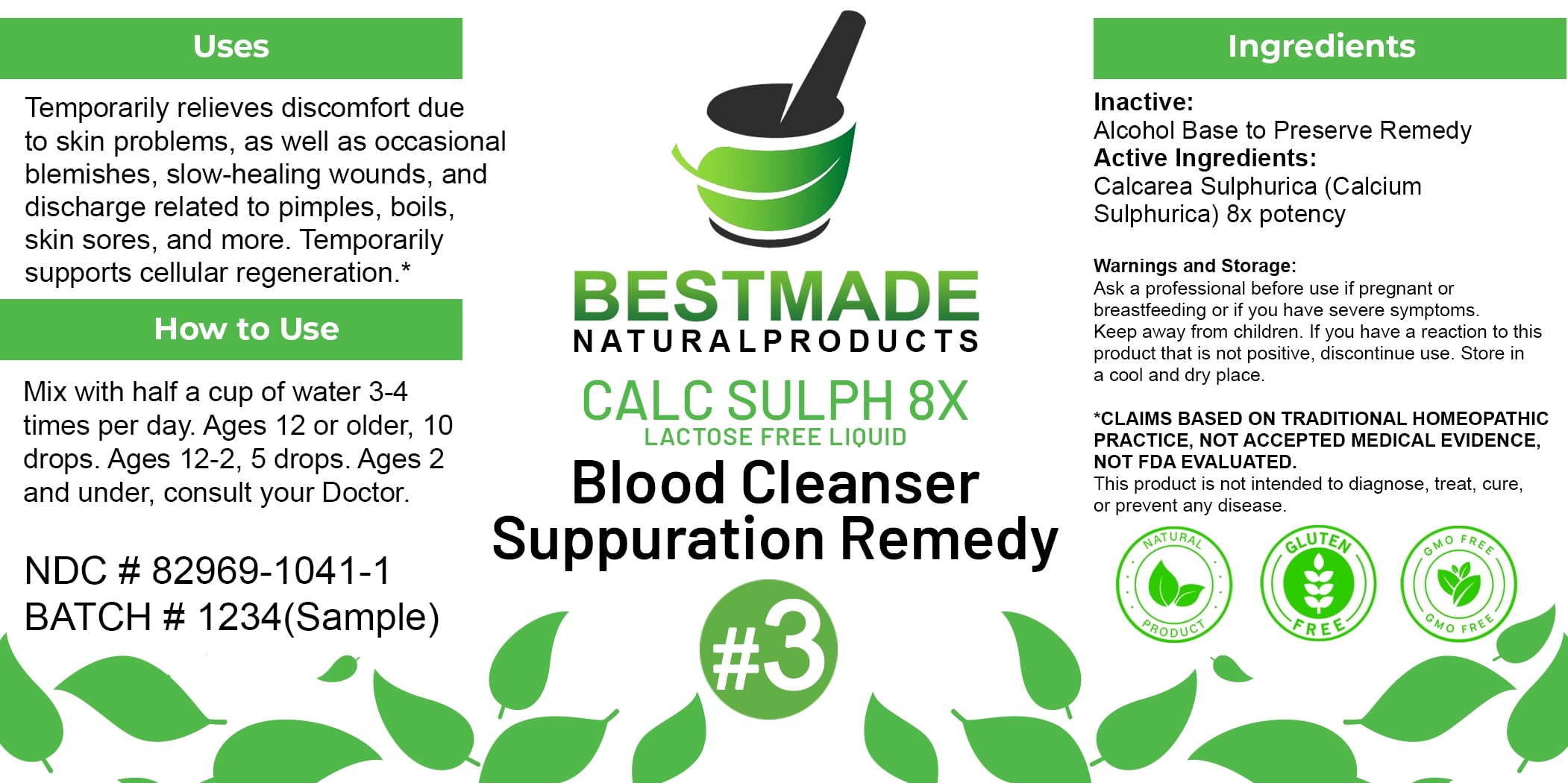 DRUG LABEL: Bestmade Natural Products Calc Sulph 8x
NDC: 82969-1041 | Form: LIQUID
Manufacturer: Bestmade Natural Products
Category: homeopathic | Type: HUMAN OTC DRUG LABEL
Date: 20250403

ACTIVE INGREDIENTS: CALCIUM SULFATE ANHYDROUS 8 [hp_X]/8 [hp_X]
INACTIVE INGREDIENTS: ALCOHOL 8 [hp_X]/8 [hp_X]

Calc Sulph 8x - liquid lactose free

DOSAGE AND ADMINISTRATION

How to Use

Mix with half a cup of water 3-4 times per day. Ages 12 or older, 10 drops. Ages 12-2, 5 drops. Ages 2 and under, consult your Doctor.

Inactive:

Alcohol Base to Preserve Product

Active Ingredients:
Calcarea Sulphurica (Calcium Sulphurica) 8x potency

Uses

Temporarily relieves discomfort due to skin problems, as well as occasional blemishes, slow-healing wounds, and discharge related to pimples, boils, skin sores, and more. Temporarily supports cellular regeneration.*

*CLAIMS BASED ON TRADITIONAL HOMEOPATHIC PRACTICE, NOT ACCEPTED MEDICAL EVIDENCE NOT FDA EVALUATED.

This product is not intended to diagnose, treat, cure, or prevent any disease.

Uses

Temporarily relieves discomfort due to skin problems, as well as occasional blemishes, slow-healing wounds, and discharge related to pimples, boils, skin sores, and more. Temporarily supports cellular regeneration.*

*CLAIMS BASED ON TRADITIONAL HOMEOPATHIC PRACTICE, NOT ACCEPTED MEDICAL EVIDENCE NOT FDA EVALUATED.

This product is not intended to diagnose, treat, cure, or prevent any disease.

KEEP OUT OF REACH OF CHILDREN

Warnings and Storage:

Ask a professional before use if pregnant or breastfeeding or if you have severe symptoms. Keep away from children. If you have a reaction to this product that is not positive, discontinue use. Store in a cool and dry place.

Warnings and Storage:

Ask a professional before use if pregnant or breastfeeding or if you have severe symptoms. Keep away from children. If you have a reaction to this product that is not positive, discontinue use. Store in a cool and dry place.

*CLAIMS BASED ON TRADITIONAL HOMEOPATHIC PRACTICE, NOT ACCEPTED MEDICAL EVIDENCE NOT FDA EVALUATED.

This product is not intended to diagnose, treat, cure, or prevent any disease.

Entire package label